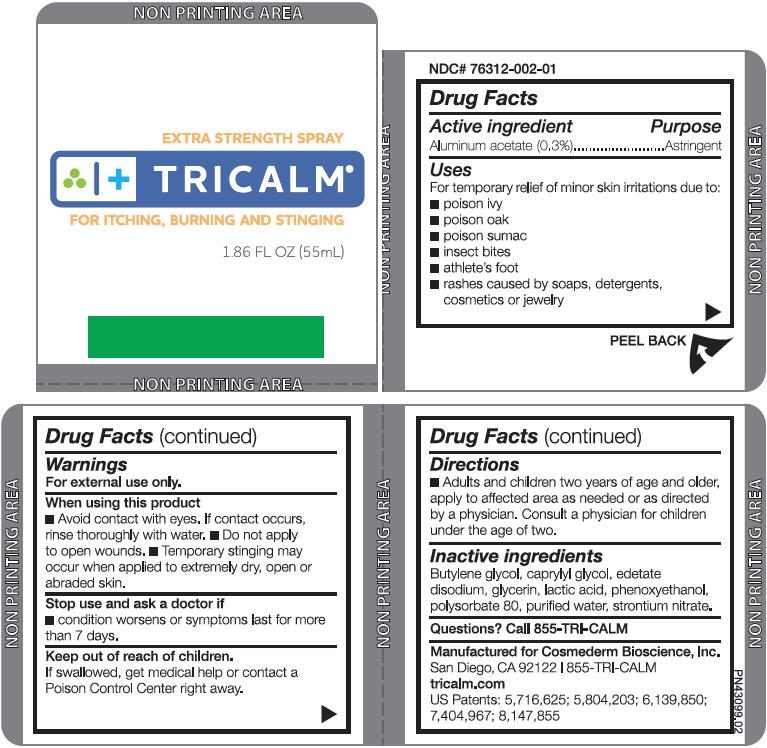 DRUG LABEL: TriCalm 
NDC: 76312-002 | Form: SOLUTION
Manufacturer: Cosmederm Bioscience
Category: otc | Type: HUMAN OTC DRUG LABEL
Date: 20150701

ACTIVE INGREDIENTS: Aluminum Acetate 3 mg/1 mL
INACTIVE INGREDIENTS: BUTYLENE GLYCOL; CAPRYLYL GLYCOL; EDETATE DISODIUM; GLYCERIN; LACTIC ACID; PHENOXYETHANOL; POLYSORBATE 80; WATER; STRONTIUM NITRATE

TriCalm®
Extra Strength Spray

Drug Facts

Active ingredient

Aluminum acetate (0.3%)

Purpose

Astringent

Uses

For temporary relief of minor skin irritations due to:

- poison ivy
- poison oak
- poison sumac
- insect bites
- athlete's foot n
- rashes caused by soaps, detergents, cosmetics or jewelry

Warnings

For external use only.

When using this product

- Avoid contact with eyes. If contact occurs, rinse thoroughly with water.
- Do not apply to open wounds.
- Temporary stinging may occur when applied to extremely dry, open or abraded skin.

Stop use and ask a doctor if

- condition worsens or symptoms last for more than 7 days.

Keep out of reach of children.

- If swallowed, get medical help or contact a Poison Control Center right away.

Directions

- Adults and children two years of age and older, apply to affected area as needed or as directed by a physician. Consult a physician for children under the age of two.

Inactive ingredients

Butylene glycol, caprylyl glycol, edetate disodium, glycerin, lactic acid, phenoxyethanol, polysorbate 80, purified water, strontium nitrate.

Questions?

Call 855-TRI-CALM

PRINCIPAL DISPLAY PANEL - 55 mL Tube Box

EXTRA STRENGTH SPRAY

TRICALM®

FOR ITCHING, BURNING AND STINGING

1.86 FL OZ (55mL)